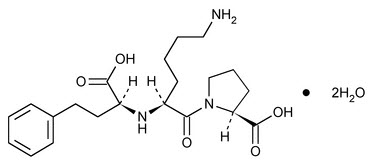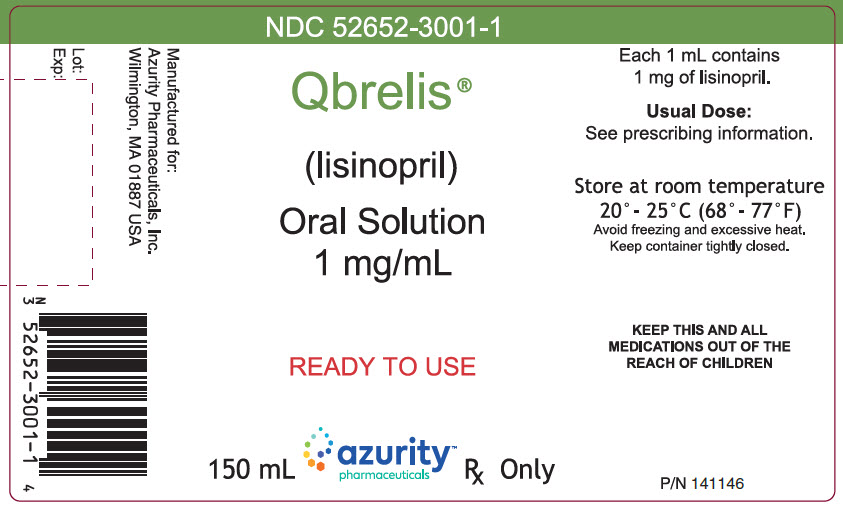 DRUG LABEL: Qbrelis
NDC: 59368-406 | Form: SOLUTION
Manufacturer: Praxis, LLC
Category: prescription | Type: HUMAN PRESCRIPTION DRUG LABEL
Date: 20230101

ACTIVE INGREDIENTS: LISINOPRIL 1 mg/1 mL
INACTIVE INGREDIENTS: WATER; XYLITOL; SODIUM CITRATE, UNSPECIFIED FORM; CITRIC ACID MONOHYDRATE; SODIUM BENZOATE; HYDROCHLORIC ACID; SODIUM HYDROXIDE

QBRELIS (lisinopril) oral solution

10 OVERDOSAGE

Following a single oral dose of 20 g/kg no lethality occurred in rats, and death occurred in one of 20 mice receiving the same dose. The most likely manifestation of overdosage would be hypotension, for which the usual treatment would be intravenous infusion of normal saline solution.

Lisinopril can be removed by hemodialysis [see Clinical Pharmacology (12.3)] .

11 DESCRIPTION

Lisinopril is an oral long-acting angiotensin converting enzyme (ACE) inhibitor. Lisinopril is a synthetic peptide derivative that is manufactured as a dihydrate and is chemically described as 1-[ N^2-[(S)-1-Carboxy-3-phenylpropyl]-L-lysyl]-L-proline dihydrate. Its molecular formula is C21H31N3O5·2H2O and its structural formula is:

Lisinopril is a white to off-white, crystalline powder, with a molecular weight of 441.52 (for dihydrate). It is soluble in water, sparingly soluble in methanol, and practically insoluble in ethanol.

QBRELIS (lisinopril), 1 mg/mL, is a ready-to-use aqueous formulation. Each 1 mL of the oral solution contains 1.09 mg of lisinopril dihydrate, which is equivalent to 1 mg of lisinopril as the active ingredient and the following inactive ingredients: purified water, xylitol, sodium citrate, citric acid, sodium benzoate, and either hydrochloric acid or sodium hydroxide which may be added for pH adjustment. The solution is clear to slightly opalescent. The pH of the solution ranges from 4.3 to 5.1. QBRELIS is supplied as 150 mL of the solution packaged in a 150-mL round, white, opaque, high-density polyethylene (HDPE) bottle with a white, polypropylene, child-resistant closure with a heat induction layered inner seal.

12 CLINICAL PHARMACOLOGY

12.1 Mechanism of Action

Lisinopril inhibits angiotensin-converting enzyme (ACE) in human subjects and animals. ACE is a peptidyl dipeptidase that catalyzes the conversion of angiotensin I to the vasoconstrictor substance, angiotensin II. Angiotensin II also stimulates aldosterone secretion by the adrenal cortex. The beneficial effects of lisinopril in hypertension and heart failure appear to result primarily from suppression of the renin-angiotensin-aldosterone system. Inhibition of ACE results in decreased plasma angiotensin II which leads to decreased vasopressor activity and to decreased aldosterone secretion. The latter decrease may result in a small increase of serum potassium. In hypertensive patients with normal renal function treated with lisinopril alone for up to 24 weeks, the mean increase in serum potassium was approximately 0.1 mEq/L; however, approximately 15% of patients had increases greater than 0.5 mEq/L and approximately 6% had a decrease greater than 0.5 mEq/L. In the same study, patients treated with lisinopril and hydrochlorothiazide for up to 24 weeks had a mean decrease in serum potassium of 0.1 mEq/L; approximately 4% of patients had increases greater than 0.5 mEq/L and approximately 12% had a decrease greater than 0.5 mEq/L [see Clinical Studies (14.1)] . Removal of angiotensin II negative feedback on renin secretion leads to increased plasma renin activity.

ACE is identical to kininase, an enzyme that degrades bradykinin. Whether increased levels of bradykinin, a potent vasodepressor peptide, play a role in the therapeutic effects of QBRELIS remains to be elucidated.

While the mechanism through which QBRELIS lowers blood pressure is believed to be primarily suppression of the renin-angiotensin-aldosterone system, QBRELIS is antihypertensive even in patients with low-renin hypertension. Although lisinopril was antihypertensive in all races studied, Black hypertensive patients (usually a low‑renin hypertensive population) had a smaller average response to monotherapy than non-Black patients.

Concomitant administration of lisinopril and hydrochlorothiazide further reduced blood pressure in Black and non-Black patients and any racial differences in blood pressure response were no longer evident.

12.2 Pharmacodynamics

Hypertension

Adult Patients: Administration of lisinopril to patients with hypertension results in a reduction of both supine and standing blood pressure to about the same extent with no compensatory tachycardia. Symptomatic postural hypotension is usually not observed although it can occur and should be anticipated in volume and/or salt-depleted patients [see Warnings and Precautions (5.4)] . When given together with thiazide-type diuretics, the blood pressure lowering effects of the two drugs are approximately additive.

In most patients studied, onset of antihypertensive activity was seen at one hour after oral administration of an individual dose of lisinopril, with peak reduction of blood pressure achieved by 6 hours. Although an antihypertensive effect was observed 24 hours after dosing with recommended single daily doses, the effect was more consistent and the mean effect was considerably larger in some studies with doses of 20 mg or more than with lower doses; however, at all doses studied, the mean antihypertensive effect was substantially smaller 24 hours after dosing than it was 6 hours after dosing.

The antihypertensive effects of lisinopril are maintained during long-term therapy. Abrupt withdrawal of lisinopril has not been associated with a rapid increase in blood pressure, or a significant increase in blood pressure compared to pretreatment levels.

Non-Steroidal Anti-Inflammatory Agents

In a study in 36 patients with mild to moderate hypertension where the antihypertensive effects of lisinopril alone were compared lisinopril given concomitantly with indomethacin, the use of indomethacin was associated with a reduced effect, although the difference between the two regimens was not significant.

12.3 Pharmacokinetics

Adult Patients: QBRELIS is bioequivalent to lisinopril tablets under fasted and fed conditions.

Following oral administration of lisinopril tablets, peak serum concentrations of lisinopril occur within about 7 hours, although there was a trend to a small delay in time taken to reach peak serum concentrations in acute myocardial infarction patients. Food does not alter the bioavailability of lisinopril tablets. Declining serum concentrations exhibit a prolonged terminal phase, which does not contribute to drug accumulation. This terminal phase probably represents saturable binding to ACE and is not proportional to dose. Upon multiple dosing, lisinopril exhibits an effective half-life of 12 hours.

Lisinopril does not appear to be bound to other serum proteins. Lisinopril does not undergo metabolism and is excreted unchanged entirely in the urine. Based on urinary recovery, the mean extent of absorption of lisinopril is approximately 25%, with large intersubject variability (6‑60%) at all doses tested (5‑80 mg). The absolute bioavailability of lisinopril is reduced to 16% in patients with stable NYHA Class II-IV congestive heart failure, and the volume of distribution appears to be slightly smaller than that in normal subjects. The oral bioavailability of lisinopril in patients with acute myocardial infarction is similar to that in healthy volunteers.

Impaired renal function decreases elimination of lisinopril, which is excreted principally through the kidneys, but this decrease becomes clinically important only when the glomerular filtration rate is below 30 mL/min. Above this glomerular filtration rate, the elimination half-life is little changed. With greater impairment, however, peak and trough lisinopril levels increase, time to peak concentration increases and time to attain steady state is prolonged [see Dosage and Administration (2.4)] . Lisinopril can be removed by hemodialysis.

Pediatric Patients:The pharmacokinetics of lisinopril were studied in 29 pediatric hypertensive patients between 6 years and 16 years with glomerular filtration rate > 30 mL/min/1.73 m^2. After doses of 0.1 to 0.2 mg per kg, steady state peak plasma concentrations of lisinopril occurred within 6 hours and the extent of absorption based on urinary recovery was about 28%. These values are similar to those obtained previously in adults. The typical value of lisinopril oral clearance (systemic clearance/absolute bioavailability) in a child weighing 30 kg is 10 L/h, which increases in proportion to renal function.

13 NONCLINICAL TOXICOLOGY

13.1 Carcinogenesis, Mutagenesis, Impairment of Fertility

There was no evidence of a tumorigenic effect when lisinopril was administered for 105 weeks to male and female rats at doses up to 90 mg per kg per day (about 56 or 9 times* the maximum recommended daily human dose, based on body weight and body surface area, respectively). There was no evidence of carcinogenicity when lisinopril was administered for 92 weeks to (male and female) mice at doses up to 135 mg per kg per day (about 84 times* the maximum recommended daily human dose). This dose was 6.8 times the maximum human dose based on body surface area in mice.

Lisinopril was not mutagenic in the Ames microbial mutagen test with or without metabolic activation. It was also negative in a forward mutation assay using Chinese hamster lung cells. Lisinopril did not produce single strand DNA breaks in an in vitroalkaline elution rat hepatocyte assay. In addition, lisinopril did not produce increases in chromosomal aberrations in an in vitrotest in Chinese hamster ovary cells or in an in vivostudy in mouse bone marrow.

There were no adverse effects on reproductive performance in male and female rats treated with up to 300 mg per kg per day of lisinopril. This dose is 188 times and 30 times the maximum human dose when based on mg/kg and mg/m^2, respectively.

Studies in rats indicate that lisinopril crosses the blood brain barrier poorly. Multiple doses of lisinopril in rats do not result in accumulation in any tissues. Milk of lactating rats contains radioactivity following administration of^14C lisinopril. By whole body autoradiography, radioactivity was found in the placenta following administration of labeled drug to pregnant rats, but none was found in the fetuses.

*Calculations assume a human weight of 50 kg and human body surface area of 1.62 m^2.

14 CLINICAL STUDIES

14.1 Hypertension

Two dose-response studies utilizing a once-daily regimen were conducted in 438 mild to moderate hypertensive patients not on a diuretic. Blood pressure was measured 24 hours after dosing. An antihypertensive effect of lisinopril was seen with 5 mg of lisinopril in some patients. However, in both studies blood pressure reduction occurred sooner and was greater in patients treated with 10, 20 or 80 mg of lisinopril than patients treated with 5 mg of lisinopril.

In controlled clinical studies of patients with mild to moderate hypertension, patients were treated with lisinopril 20-80 mg daily, hydrochlorothiazide 12.5-50 mg daily or atenolol 50‑200 mg daily; and in other studies of patients with moderate to severe hypertension, patients were treated with lisinopril 20-80 mg daily or metoprolol 100-200 mg daily. Lisinopril demonstrated superior reductions of systolic and diastolic compared to hydrochlorothiazide in a population that was 75% Caucasian. Lisinopril was approximately equivalent to atenolol and metoprolol in reducing diastolic blood pressure, and had somewhat greater effects on systolic blood pressure.

Lisinopril had similar blood pressure reductions and adverse effects in younger and older (> 65 years) patients. It was less effective in reducing blood pressure in Blacks than in Caucasians.

In hemodynamic studies of lisinopril in patients with essential hypertension, blood pressure reduction was accompanied by a reduction in peripheral arterial resistance with little or no change in cardiac output and in heart rate. In a study in nine hypertensive patients, following administration of lisinopril, there was an increase in mean renal blood flow that was not significant. Data from several small studies are inconsistent with respect to the effect of lisinopril on glomerular filtration rate in hypertensive patients with normal renal function, but suggest that changes, if any, are not large.

In patients with renovascular hypertension lisinopril has been shown to be well-tolerated and effective in reducing blood pressure [see Warnings and Precautions (5.3)] .

Pediatric Patients:In a clinical study involving 115 hypertensive pediatric patients 6 to 16 years of age, patients who weighed < 50 kg received either 0.625, 2.5 or 20 mg of lisinopril once daily and patients who weighed ≥ 50 kg received either 1.25, 5, or 40 mg of lisinopril once daily. At the end of 2 weeks, lisinopril lowered trough blood pressure in a dose-dependent manner with antihypertensive efficacy demonstrated at doses > 1.25 mg (0.02 mg per kg). This effect was confirmed in a randomized withdrawal phase, where the diastolic pressure rose by about 9 mmHg more in patients randomized to placebo than compared to patients who remained on the middle and high doses of lisinopril. The dose-dependent antihypertensive effect of lisinopril was consistent across several demographic subgroups: age, Tanner stage, gender, and race. In this study, lisinopril was generally well-tolerated.

In the above pediatric study, lisinopril was given either as tablets or in a suspension for those children who were unable to swallow tablets or who required a lower dose than is available in tablet form.

14.2 Heart Failure

Two placebo controlled, 12-week clinical studies compared the addition of lisinopril up to 20 mg daily to digitalis and diuretics alone. The combination of lisinopril, digitalis and diuretics reduced the following signs and symptoms of heart failure: edema, rales, paroxysmal nocturnal dyspnea and jugular venous distention. In one of the studies, the combination of lisinopril, digitalis and diuretics reduced orthopnea, presence of third heart sound and the number of patients classified as NYHA Class III and IV; and improved exercise tolerance. A large (over 3000 patients) survival study, the ATLAS Trial, comparing 2.5 and 35 mg of lisinopril in patients with systolic heart failure, showed that the higher dose of lisinopril had outcomes at least as favorable as the lower dose.

During baseline-controlled clinical trials, in patients with systolic heart failure receiving digitalis and diuretics, single doses of lisinopril resulted in decreases in pulmonary capillary wedge pressure, systemic vascular resistance and blood pressure accompanied by an increase in cardiac output and no change in heart rate.

14.3 Acute Myocardial Infarction

The Gruppo Italiano per lo Studio della Sopravvienza nell’Infarto Miocardico (GISSI-3) study was a multicenter, controlled, randomized, unblinded clinical trial conducted in 19,394 patients with acute myocardial infarction (MI) admitted to a coronary care unit. It was designed to examine the effects of short-term (6 week) treatment with lisinopril, nitrates, their combination, or no therapy on short-term (6 week) mortality and on long-term death and markedly impaired cardiac function. Hemodynamically-stable patients presenting within 24 hours of the onset of symptoms were randomized, in a 2 x 2 factorial design, to six weeks of either 1) lisinopril alone (n=4841), 2) nitrates alone (n=4869), 3) lisinopril plus nitrates (n=4841), or 4) open control (n=4843). All patients received routine therapies, including thrombolytics (72%), aspirin (84%), and a beta blocker (31%), as appropriate, normally utilized in acute myocardial infarction (MI) patients.

The protocol excluded patients with hypotension (systolic blood pressure ≤ 100 mmHg), severe heart failure, cardiogenic shock, and renal dysfunction (serum creatinine > 2 mg per dL and/or proteinuria > 500 mg per 24 h). Patients randomized to lisinopril received 5 mg within 24 hours of the onset of symptoms, 5 mg after 24 hours, and then 10 mg daily thereafter. Patients with systolic blood pressure less than 120 mmHg at baseline received 2.5 mg of lisinopril. If hypotension occurred, the lisinopril dose was reduced or if severe hypotension occurred lisinopril was stopped [see Dosage and Administration (2.3)] .

The primary outcomes of the trial were the overall mortality at 6 weeks and a combined end point at 6 months after the myocardial infarction, consisting of the number of patients who died, had late (day 4) clinical congestive heart failure, or had extensive left ventricular damage defined as ejection fraction ≤ 35% or an akinetic-dyskinetic [A-D] score ≥ 45%. Patients receiving lisinopril (n=9646), alone or with nitrates, had an 11% lower risk of death (p=0.04) compared to patients who did not receive lisinopril (n=9672) (6.4% vs. 7.2%, respectively) at six weeks. Although patients randomized to receive lisinopril for up to six weeks also fared numerically better on the combined end point at 6 months, the open nature of the assessment of heart failure, substantial loss to follow-up echocardiography, and substantial excess use of lisinopril between 6 weeks and 6 months in the group randomized to 6 weeks of lisinopril, preclude any conclusion about this end point.

Patients with acute myocardial infarction, treated with lisinopril, had a higher (9.0% versus 3.7%) incidence of persistent hypotension (systolic blood pressure < 90 mmHg for more than 1 hour) and renal dysfunction (2.4% versus 1.1%) in-hospital and at six weeks (increasing creatinine concentration to over 3 mg per dL or a doubling or more of the baseline serum creatinine concentration) [see Adverse Reactions (6.1)] .

16 HOW SUPPLIED/STORAGE AND HANDLING

QBRELIS (lisinopril), 1 mg/mL, is supplied as 150 mL of a clear to slightly opalescent, colorless aqueous oral solution with a sweet taste in a 150-mL high-density polyethylene (HDPE) bottle with a child-resistant cap (NDC 52652-3001-1).

Store at controlled room temperature 20°C-25°C (68°F-77°F) [see USP] in a tightly closed container. Protect from freezing and excessive heat.

17 PATIENT COUNSELING INFORMATION

Pregnancy: Tell female patients of childbearing age about the consequences of exposure to QBRELIS during pregnancy. Discuss treatment options with women planning to become pregnant. Tell patients to report pregnancies to their physicians as soon as possible.

Angioedema: Angioedema, including laryngeal edema may occur at any time during treatment with angiotensin converting enzyme inhibitors, including QBRELIS. Tell patients to report immediately any signs or symptoms suggesting angioedema (swelling of face, extremities, eyes, lips, tongue, difficulty swallowing or breathing) and to take no more drug until they have consulted with the prescribing physician.

Symptomatic Hypotension: Tell patients to report light-headedness especially during the first few days of therapy. If actual syncope occurs, tell the patient to discontinue the drug until they have consulted with the prescribing physician.

Tell patients that excessive perspiration and dehydration may lead to an excessive fall in blood pressure because of reduction in fluid volume. Other causes of volume depletion such as vomiting or diarrhea may also lead to a fall in blood pressure; advise patients accordingly.

Hyperkalemia: Tell patients to consult their physician prior to using salt substitutes containing potassium.

Hypoglycemia: Tell diabetic patients treated with oral antidiabetic agents or insulin starting an ACE inhibitor to monitor for hypoglycemia closely, especially during the first month of combined use [see Drug Interactions (7.2)] .

Leukopenia/Neutropenia: Tell patients to report promptly any indication of infection (e.g., sore throat, fever), which may be a sign of leukopenia/neutropenia.

Manufactured for:
Azurity Pharmaceuticals, Inc.
Woburn, MA 01801 USA

Patent: https://azurity.com/patents

This product’s label may have been updated. For current Full Prescribing Information, please visit Qbrelis.com

PI100073.05 Rev. 4/2023

PRINCIPAL DISPLAY PANEL - Bottle Label

NDC 52652-3001-1

Qbrelis®
(lisinopril)

Oral Solution
1 mg/mL

READY TO USE

150 mL
azurity™
pharmaceuticals
Rx Only

Each 1 mL contains
1 mg of lisinopril.

Usual Dose:
See prescribing information.

Store at room temperature
20° - 25°C (68° - 77°F)
Avoid freezing and excessive heat.
Keep container tightly closed.

KEEP THIS AND ALL
MEDICATIONS OUT OF THE
REACH OF CHILDREN

P/N 141146

Manufactured for:
Azurity Pharmaceuticals, Inc.
Wilmington, MA 01887 USA

Lot:
Exp: